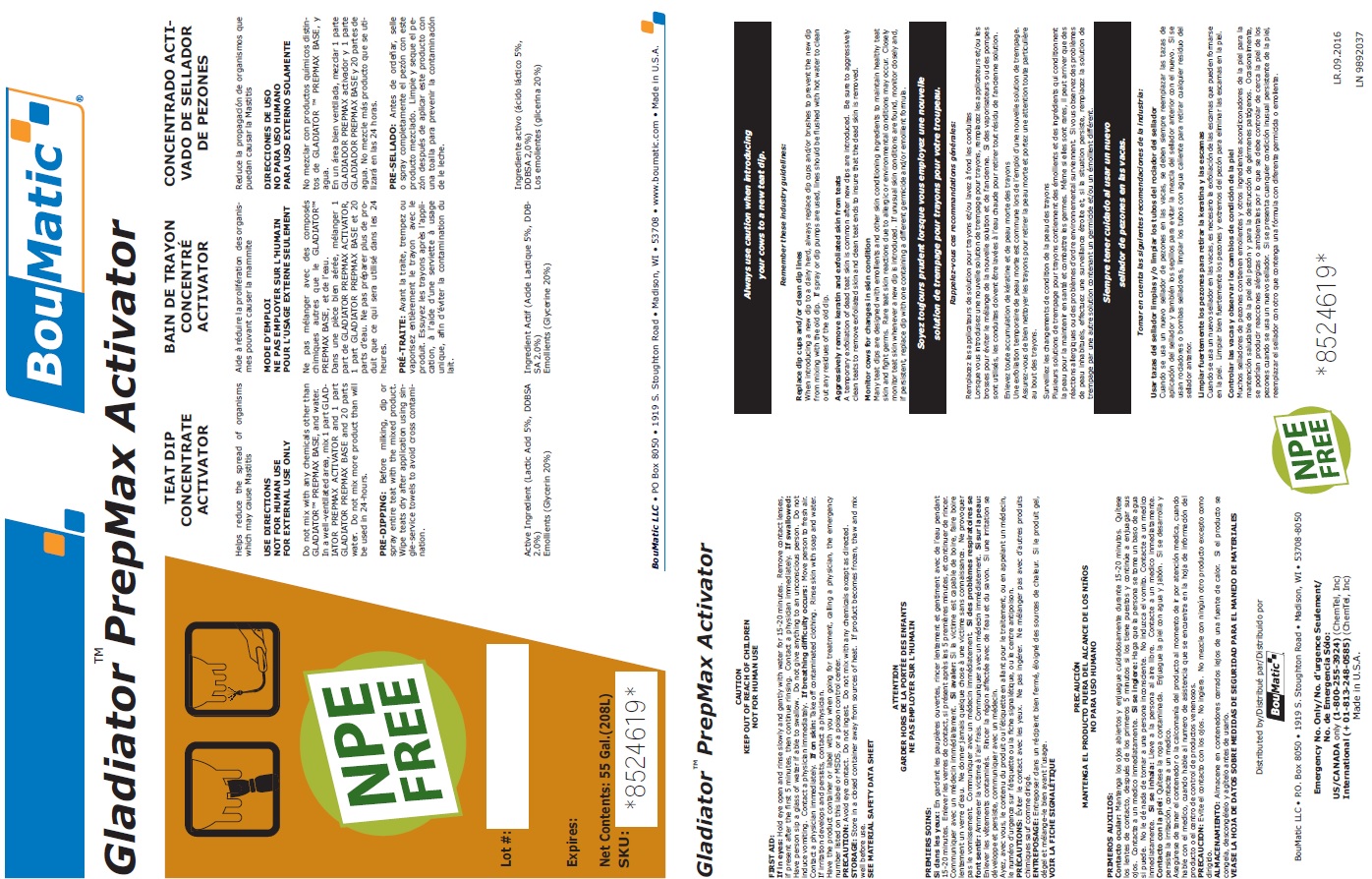 DRUG LABEL: Gladiator PrepMax Activator
NDC: 48106-2030 | Form: LIQUID
Manufacturer: BouMatic, LLC
Category: animal | Type: OTC ANIMAL DRUG LABEL
Date: 20240614

ACTIVE INGREDIENTS: LACTIC ACID 50 g/1 L
INACTIVE INGREDIENTS: GLYCERIN 200 g/1 L

Gladiator PrepMax Activator

WARNINGS AND PRECAUTIONS

CAUTION

KEEP OUT OF REACH OF CHILDREN

NOT FOR HUMAN USE

FIRST AID:

If in eyes:Hold eye open and rinse slowly and gently with water for 15-20 minutes. Remove contact lenses, if present after the first 5 minutes, then continue rinsing. Contact a physician immediately. If swallowed: Have person sip a glass of water if able to swallow. Do not give anything to an unconscious person. Do not induce vomiting. Contact a physician immediately. If breathing difficulty occurs: Move person to fresh air. Contact a physician immediately. If on skin: Take off contaminated clothing. Rinse skin with soap and water. If irritation develops and persists, contact a physician.

Have the product container or label with you when going for treatment, calling a physician, the emergency number listed on this label or MSDS, or a poison control center.

PRECAUTION:

Avoid eye contact. Do not ingest. Do not mix with any chemicals except as directed.

STORAGE:

Store in a closed container away from sources of heat. If product becomes frozen, thaw and mix well before use.

SEE MATERIAL SAFETY DATA SHEET

INDICATIONS AND USAGE

Helps reduce the spread of organisms which may cause Mastitis

USE DIRECTIONS

NOT FOR HUMAN USE

FOR EXTERNAL USE ONLY

Do not mix with any chemicals other than GLADIATOR™ PREPMAX BASE, and water.

In a well-ventilated area, mix 1 part GLADIATOR PREPMAX ACTIVATOR and 1 part GLADIATOR PREPMAX BASE and 20 parts water. Do not mix more product than will be used in 24-hours.

PRE-DIPPING:

Before milking, dip or spray entire teat with the mixed product. Wipe teats dry after application using single-service towels to avoid cross contamination.